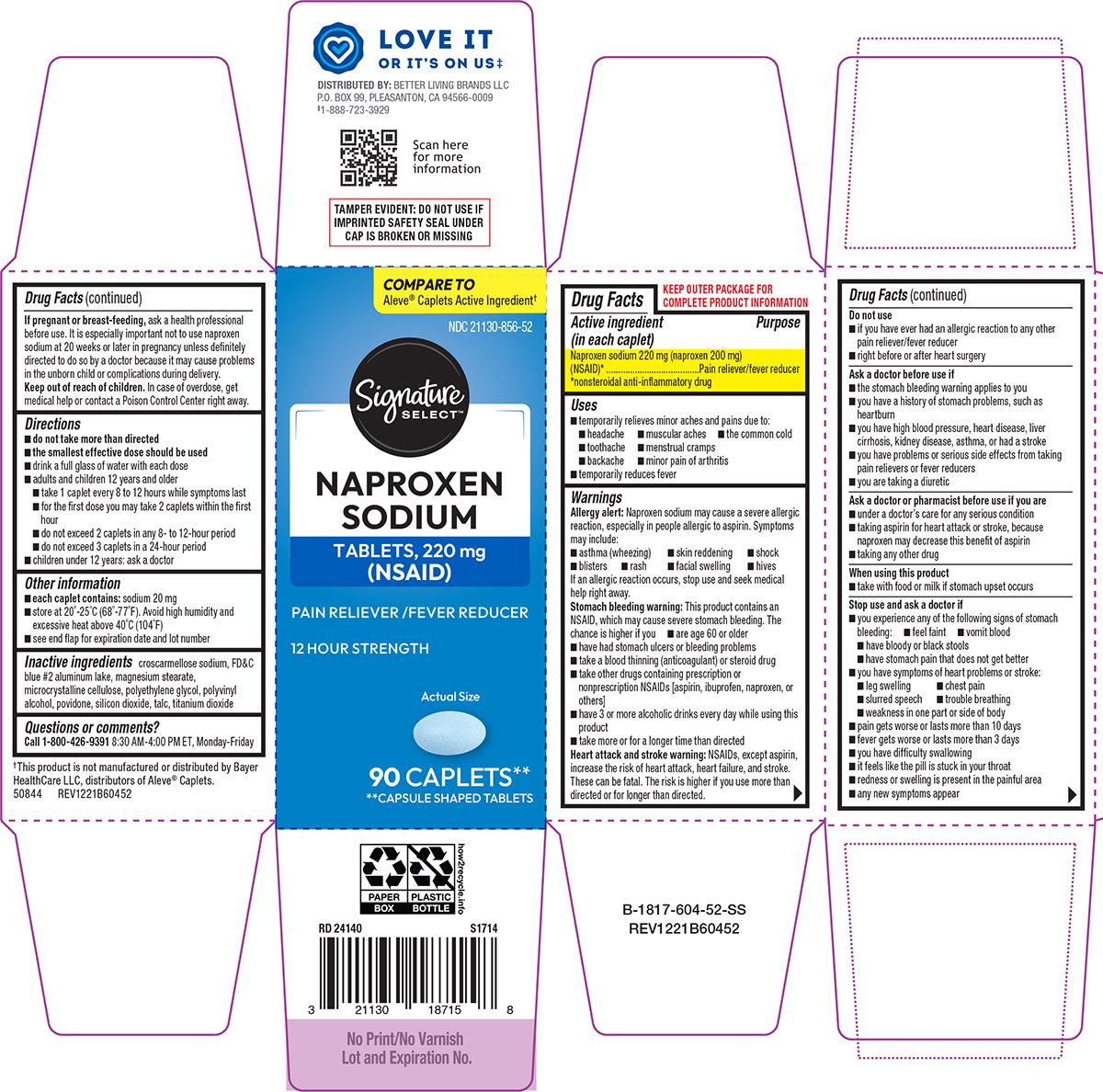 DRUG LABEL: Naproxen Sodium
NDC: 21130-856 | Form: TABLET, FILM COATED
Manufacturer: Better Living Brands, LLC
Category: otc | Type: HUMAN OTC DRUG LABEL
Date: 20260213

ACTIVE INGREDIENTS: NAPROXEN SODIUM 220 mg/1 1
INACTIVE INGREDIENTS: CROSCARMELLOSE SODIUM; FD&C BLUE NO. 2 ALUMINUM LAKE; MAGNESIUM STEARATE; MICROCRYSTALLINE CELLULOSE; POLYETHYLENE GLYCOL, UNSPECIFIED; POLYVINYL ALCOHOL, UNSPECIFIED; POVIDONE, UNSPECIFIED; SILICON DIOXIDE; TALC; TITANIUM DIOXIDE

Signature Select 44-604

Active ingredient (in each caplet)

Naproxen sodium 220 mg (naproxen 200 mg) (NSAID)*
*nonsteroidal anti-inflammatory drug

Purpose

Pain reliever/fever reducer

Uses

- temporarily relieves minor aches and pains due to:
  - headache
  - muscular aches
  - the common cold
  - toothache
  - backache
  - menstrual cramps
  - minor pain of arthritis
- temporarily reduces fever

Warnings

Allergy alert: Naproxen sodium may cause a severe allergic reaction, especially in people allergic to aspirin. Symptoms may include:

- asthma (wheezing)
- skin reddening
- shock
- blisters
- rash
- facial swelling
- hives

If an allergic reaction occurs, stop use and seek medical help right away.

Stomach bleeding warning: This product contains an NSAID, which may cause severe stomach bleeding. The chance is higher if you

- have had stomach ulcers or bleeding problems
- take a blood thinning (anticoagulant) or steroid drug
- take other drugs containing prescription or nonprescription NSAIDs [aspirin, ibuprofen, naproxen, or others]
- are age 60 or older
- have 3 or more alcoholic drinks every day while using this product
- take more or for a longer time than directed

Heart attack and stroke warning: NSAIDs, except aspirin, increase the risk of heart attack, heart failure, and stroke. These can be fatal. The risk is higher if you use more than directed or for longer than directed.

Do not use

- if you have ever had an allergic reaction to any other pain reliever/fever reducer
- right before or after heart surgery

Ask a doctor before use if

- the stomach bleeding warning applies to you
- you have a history of stomach problems, such as heartburn
- you are taking a diuretic
- you have high blood pressure, heart disease, liver cirrhosis, kidney disease, asthma, or had a stroke
- you have problems or serious side effects from taking pain relievers or fever reducers

Ask a doctor or pharmacist before use if you are

- under a doctor’s care for any serious condition
- taking aspirin for heart attack or stroke, because naproxen may decrease this benefit of aspirin
- taking any other drug

When using this product

- take with food or milk if stomach upset occurs

Stop use and ask a doctor if

- you experience any of the following signs of stomach bleeding:
  - feel faint
  - vomit blood
  - have bloody or black stools
  - have stomach pain that does not get better
- you have symptoms of heart problems or stroke:
  - leg swelling
  - chest pain
  - slurred speech
  - trouble breathing
  - weakness in one part or side of body
- pain gets worse or lasts more than 10 days
- fever gets worse or lasts more than 3 days
- you have difficulty swallowing
- it feels like the pill is stuck in your throat
- redness or swelling is present in the painful area
- any new symptoms appear

If pregnant or breast-feeding,

ask a health professional before use. It is especially important not to use naproxen sodium at 20 weeks or later in pregnancy unless definitely directed to do so by a doctor because it may cause problems in the unborn child or complications during delivery.

Keep out of reach of children.

In case of overdose, get medical help or contact a Poison Control Center right away.

Directions

- do not take more than directed
- the smallest effective dose should be used
- drink a full glass of water with each dose
- adults and children 12 years and older
  - take 1 caplet every 8 to 12 hours while symptoms last
  - for the first dose you may take 2 caplets within the first hour
  - do not exceed 2 caplets in any 8- to 12-hour period
  - do not exceed 3 caplets in a 24-hour period
- children under 12 years: ask a doctor

Other information

- each caplet contains: sodium 20 mg
- store at 20°-25°C (68°-77°F). Avoid high humidity and excessive heat above 40°C (104°F)
- see end flap for expiration date and lot number

Inactive ingredients

croscarmellose sodium, FD&C blue #2 aluminum lake, magnesium stearate, microcrystalline cellulose, polyethylene glycol, polyvinyl alcohol, povidone, silicon dioxide, talc, titanium dioxide

Questions or comments?

Call 1-800-426-9391 8:30 AM-4:00 PM ET, Monday-Friday

Principal display panel

COMPARE TO
Aleve® Caplets Active Ingredient†

NDC 21130-856-52

Signature
SELECT™

NAPROXEN
SODIUM
TABLETS, 220 mg (NSAID)
Pain Reliever/
Fever Reducer

12 HOUR STRENGTH

Actual Size

90 CAPLETS**
**CAPSULE-SHAPED TABLETS

TAMPER EVIDENT: DO NOT USE IF
IMPRINTED SAFETY SEAL UNDER
CAP IS BROKEN OR MISSING

†This product is not manufactured or distributed by Bayer
HealthCare LLC, distributors of Aleve® Caplets.
50844 REV1221B60452

♥︎ LOVE IT
OR IT'S ON US‡

DISTRIBUTED BY: BETTER LIVING BRANDS LLC
P.O. BOX 99, PLEASANTON, CA 94566-0009
‡1-888-723-3929

Scan here
for more
information

Signature Select 44-604